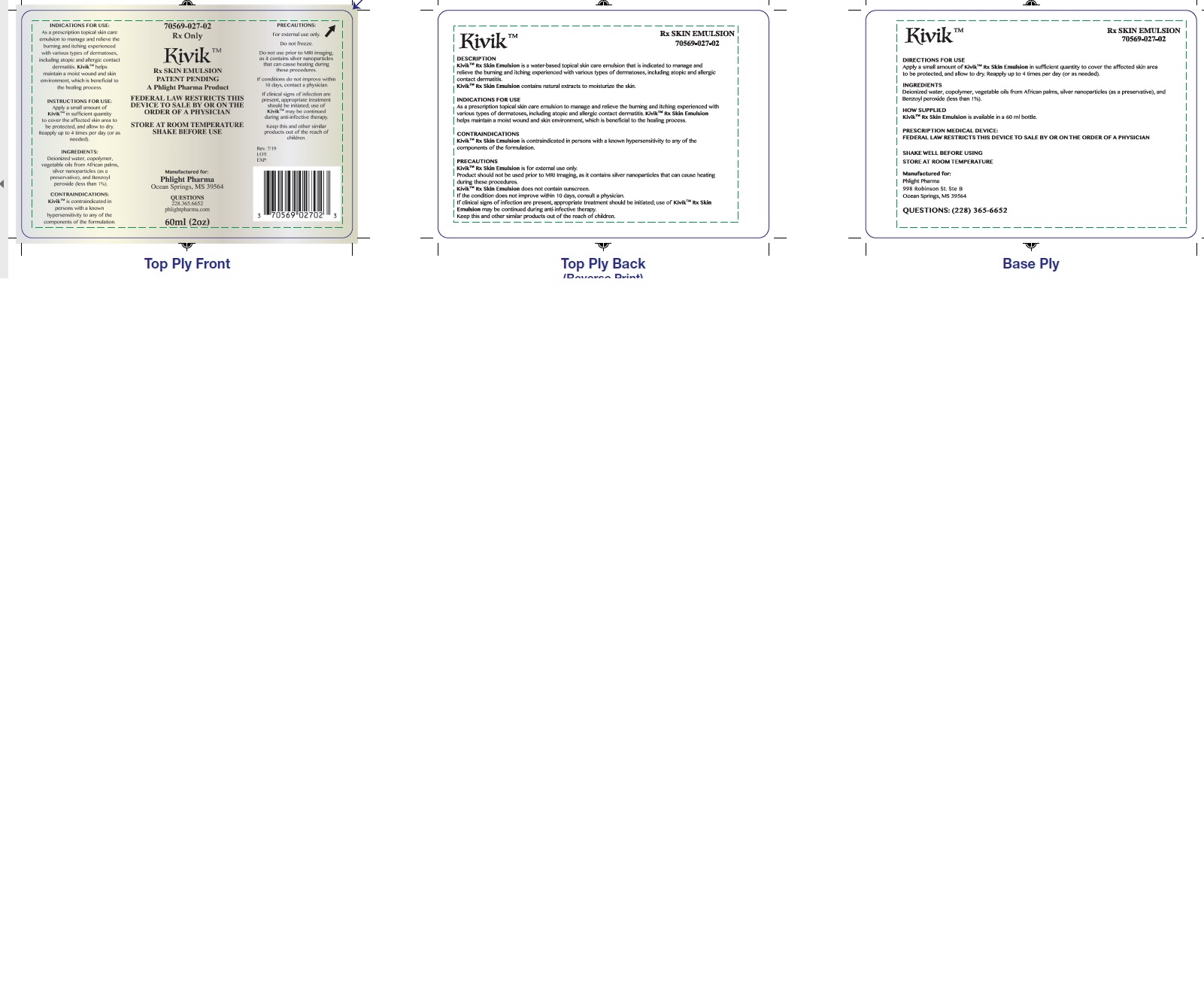 DRUG LABEL: Kivik Rx Skin Emulsion
NDC: 70569-027
Manufacturer: Phlight Pharma
Category: other | Type: PRESCRIPTION MEDICAL DEVICE LABEL
Date: 20190828

Kivik Rx Skin Emulsion

DESCRIPTION

Kivik Rx Skin Emulsion is a water-based topical skin care emulsion that is indicated to manage and relieve the burning and itching experienced with various types of dermatoses, including atopic and allergic contact dermatitis. Kivik Rx Skin Emulsion contains natural extracts to moisturize the skin.

INDICATIONS FOR USE

Kivik Rx Skin Emulsion is indicated as a prescription topical skin care emulsion to manage and relieve the burning and itching experienced with various types of dermatoses, including atopic and allergic contact dermatitis. Kivik Rx Skin Emulsion helps maintain a moist wound and skin environment, which is beneficial to the healing process.

CONTRAINDICATIONS

Kivik Rx Skin Emulsion is contraindicated in persons with a known hypersensitivity to any of the components of the formulation.

PRECAUTIONS

Kivik Rx Skin Emulsion is for external use only.
Product should not be used prior to MRI Imaging, as it contains silver nanoparticles that can cause heating during these procedures.
Kivik Rx Skin Emulsion does not contain sunscreen. If the condition does not improve within 10 days, consult a physician. If clinical signs of infection are present, appropriate treatment should be initiated; use of Kivik Rx Skin Emulsion may be continued during anti-infective therapy.
Keep this and other similar products out of the reach of children.

HOW TO APPLY

Shake well before use. Apply a small amount of Kivik Rx Skin Emulsion in sufficient quantity to cover the affected skin area to be protected, and allow to dry. Reapply up to 4 times per day (or as needed).

INGREDIENTS

Kivik Rx Skin Emulsion contains deionized water, copolymer, vegetable oils from African palms, and silver nanoparticles (as a preservative), and benzoyl peroxide (less than 1%).

HOW SUPPLIED

Kivik Rx Skin Emulsion is available in 60mL bottles, 70569-027-02.

Shake well before using.
Store at room temperature. Do not freeze.

Rx Only

For External Use Only.

PRESCRIPTION MEDICAL DEVICE:FEDERAL LAW RESTRICTS THIS DEVICE TO SALE BY OR ON THE ORDER OF A PHYSICIAN

Manufactured for:

Phlight Pharma
998 Robinson St. Ste B
Ocean Springs, MS 39564